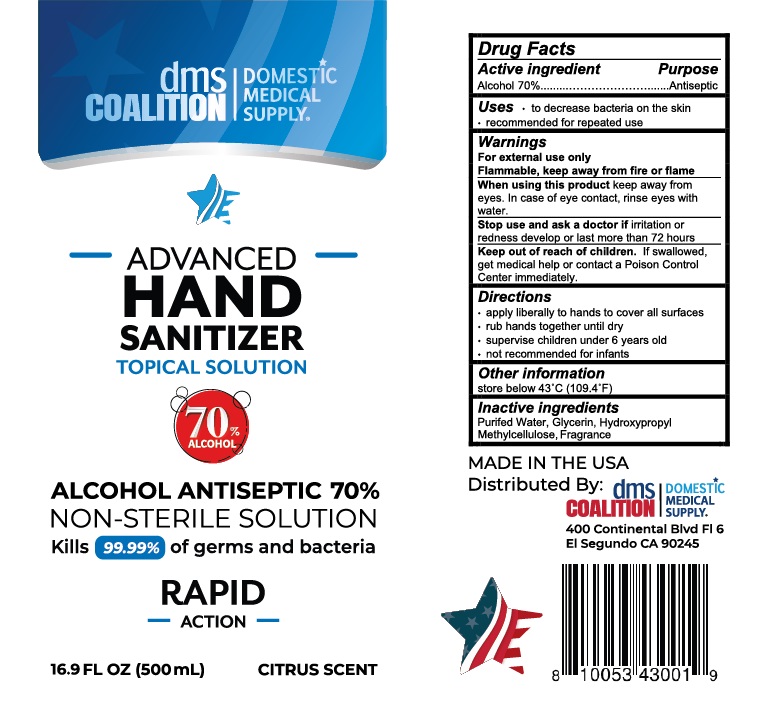 DRUG LABEL: DMS Coalition Hand Sanitizer
NDC: 79407-002 | Form: SOLUTION
Manufacturer: Domestic Medical Supply Coalition, LLC
Category: otc | Type: HUMAN OTC DRUG LABEL
Date: 20200713

ACTIVE INGREDIENTS: ALCOHOL 70 mL/100 mL
INACTIVE INGREDIENTS: HYPROMELLOSE, UNSPECIFIED; WATER; GLYCERIN

DMS Coalition Advanced Hand Sanitizer, Citrus Scent

Drug Facts

Active ingredient

Alcohol 70%

Purpose
Antiseptic

Uses

- to decrease bacteria on the skin
- recommended for repeated use

Warnings
For external use only.
Flammable. Keep away from fire or flame.

When using this product keep away from eyes. In case of eye contact, rinse eyes with water.

Stop use and ask a doctor if irritation or redness develop or last more than 72 hours.

Keep out of reach of children. If swallowed, get medical help or contact a Poison Control Center immediately.

Directions

- apply liberally to hands to cover all surfaces
- rub hands together until dry
- supervise children under 6 years old
- not recommended for infants

Other information

store below 43°C (109.4°F)

Inactive ingredients

Purified water, Glycerin, Hydroxypropyl Methylcellulose, Fragrance

Distributed by:
dms COALITION | DOMESTIC MEDICAL SUPPLY
400 Continental Blvd. Fl 6
El Segundo, CA 90245

PACKAGE LABEL

dms COALITION | DOMESTIC MEDICAL SUPPLY
ADVANCED HAND SANITIZER

TOPICAL SOLUTION
ALCOHOL ANTISEPTIC 70%
NON-STERILE SOLUTION

Kills 99.99% of germs and bacteria
RAPID ACTION
2 FL OZ (59 mL)
CITRUS SCENT